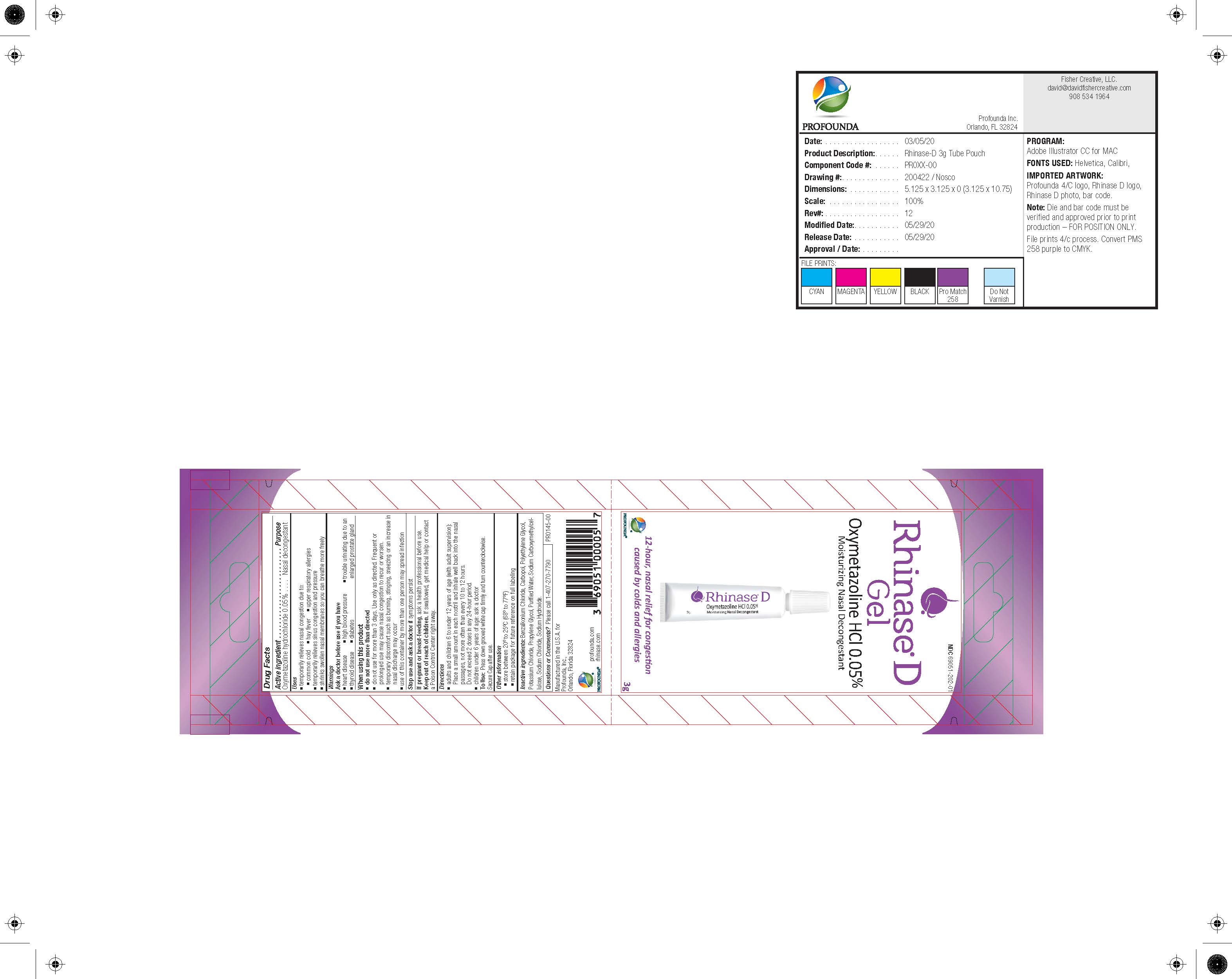 DRUG LABEL: Rhinase D Gel Moisturizing Nasal Decongestant
NDC: 69051-202 | Form: JELLY
Manufacturer: Profounda Inc
Category: otc | Type: HUMAN OTC DRUG LABEL
Date: 20251218

ACTIVE INGREDIENTS: OXYMETAZOLINE HYDROCHLORIDE 0.05 {VP}/100 {VP}
INACTIVE INGREDIENTS: CARBOXYMETHYLCELLULOSE 0.7 {VP}/100 {VP}; WATER 55.5 {VP}/100 {VP}; BENZALKONIUM CHLORIDE 0.018 {VP}/100 {VP}; POTASSIUM CHLORIDE 0.167 {VP}/100 {VP}; SODIUM CHLORIDE 0.218 {VP}/100 {VP}; POLYETHYLENE GLYCOL 10000 14.993 {VP}/100 {VP}; DIPROPYLENE GLYCOL 19.99 {VP}/100 {VP}; CARBOMER 934 1.809 {VP}/100 {VP}; SODIUM HYDROXIDE 0.308 {VP}/100 {VP}

Rhinase D (Oxymetazoline HCL) Moisturizing Nasal Decongestant 3 g

Active Ingredient........Purpose

Oxymetalozine 0.05%.....Nasal Decongestant

Stop use and ask a doctor if symptoms persist

USES

- temporarily relieves nasal congestion due to:

- common cold - Hay fever - upper respiratory allergies

- temporarily relieves sinus congestion and pressure

-shrinks swollen nasal membranes so you can breathe more freely

- do not use more than directed

- do not use for more than 3 days. Use only as directed. Frequent or prolonged use may cause nasal congestion to recur or worsen.

- temporary discomfort such as burning, stinging, sneezing or an increase in nasal discharge may occur

- use of this container by more than one person may spread infection.

PREGNANCY OR BREAST FEEDING

If pregnant or brreast feeding ask a health professional before use

Keep out of reach of children. If swallowed get medical help or contact a poisen control center right away

QUESTIONS

Please call 407-270-7790

DOSAGE AND ADMINISTRATION

Adults and Children 6 to under 12 years of age (with adult supervision) Place a small amount in each nostril and inhale well back into the nasal passages, not more often than every 10-12 hours. Do not exceed 2 doses in any 24 hour period.

children under 6 years of age ask a doctor.

To Use: press down grooved white cap firmly and turn counter clockwise . Secure cap after use.

Ask a doctor if you have - heart disease - high blood pressure - trouble urinating due to a thyroid disease - diabetes - enlarged prostrate gland

INACTIVE INGREDIENT

Inactive ingredients: Purified Water, Carbopol, Sodium Carboxymethylcellulose,
Sodium

USES

- temporarily relieves nasal congestion due to:

- common cold - Hay fever - upper respiratory allergies

- temporarily relieves sinus congestion and pressure

-shrinks swollen nasal membranes so you can breathe more freely

USES

- temporarily relieves nasal congestion due to:

- common cold - Hay fever - upper respiratory allergies

- temporarily relieves sinus congestion and pressure

-shrinks swollen nasal membranes so you can breathe more freely

RhinaseD_Sachet_3g_200422_052920-FIN.jpg

NDC 69051-202-01

Rhinase D Gel

Oxymetazoline HCL 0.05%

Moisturing Nasal Decongestant

12 hour nasal relief for congestion caused by colds and allergies

Profounda logo